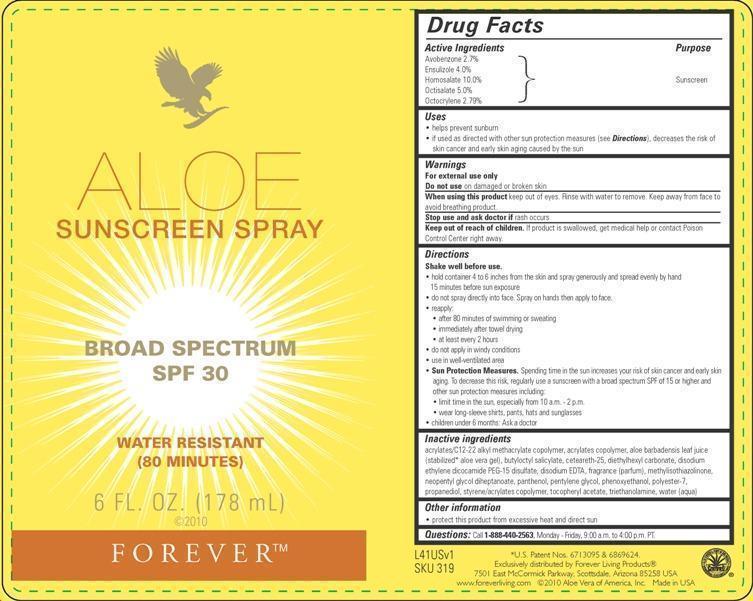 DRUG LABEL: Aloe Sunscreen
NDC: 11697-319 | Form: SPRAY
Manufacturer: Aloe Vera of America, Inc.
Category: otc | Type: HUMAN OTC DRUG LABEL
Date: 20150122

ACTIVE INGREDIENTS: HOMOSALATE 10.0 g/100 mL; OCTISALATE 5.0 g/100 mL; ENSULIZOLE 4.0 g/100 mL; AVOBENZONE 3.0 g/100 mL; OCTOCRYLENE 2.79 g/100 mL
INACTIVE INGREDIENTS: ALOE VERA LEAF 29.3 g/100 mL; WATER 27.3 g/100 mL; PROPANEDIOL 3.0 g/100 mL; DIETHYLHEXYL CARBONATE 3.0 g/100 mL; BUTYLOCTYL SALICYLATE 3.0 g/100 mL; POLYESTER-7 2.4 g/100 mL; STYRENE/ACRYLAMIDE COPOLYMER (MW 500000) 1.9 g/100 mL; NEOPENTYL GLYCOL DIHEPTANOATE 1.6 g/100 mL; CETEARETH-25 0.7 g/100 mL; PHENOXYETHANOL 0.3 g/100 mL; DISODIUM ETHYLENE DICOCAMIDE PEG-15 DISULFATE 0.3 g/100 mL; PENTYLENE GLYCOL 0.1 g/100 mL; PANTHENOL 0.1 g/100 mL; .ALPHA.-TOCOPHEROL ACETATE 0.01 g/100 mL; METHYLISOTHIAZOLINONE 0.01 g/100 mL; EDETATE DISODIUM 0.1 g/100 mL; TROLAMINE 0.3 g/100 mL

Active Ingredients Purpose

Avobenzone 2.7%

Ensulizole 4.0%

Homosalate 10.0%

Octisalate 5.0%

Octocrylene 2.79% Sunscreen

Uses

- helps prevent sunburn
- if used as directed with other sun protection measures (see Directions), decreases the risk of skin cancer and early skin aging caused by the sun

Warnings

For external use only

Do not use on damaged or broken skin

When using this product keep out of eyes. Rinse with water to remove. Keep away from face to avoid breathing product.

Stop use and ask doctor if rash occurs

Keep out of reach of children. If product is swallowed, get medical help or contact a Poison Control Center right away.

Directions

Shake well before use.

- hold container 4 to 6 inches from the skin and spray generously and spread evenly by hand 15 minutes before sun exposure
- do not spray directly into face. Spray on hands then apply to face.
- rapply:
- after 80 minutes of swimming or sweating
- immediately after towel drying
- at least every 2 hours
- do not apply in windy conditions
- use in well-ventilated area
- Sun Protection Measures. Spending time in the sun increases your risk of skin cancer and early skin aging. To decrease this risk, regularly use a sunscreen with a broad spectrum SPF of 15 or higher and other sun protection measures including:
- limit time in the sun, especially from 10 a.m. - 2 p.m.
- wear long-sleeve shirts, pants, hats and sunglasses
- children under 6 months: Ask a doctor

Inactive ingredients
acrylates/C12-22 alkyl methacrylate copolymer, acrylates copolymer, aloe barbadensis leaf juice (stabilized* aloe vera gel), butyloctyl salicylate, ceteareth-25, diethylhexyl carbonate, disodium ethylene dicocamide PEG-15 disulfate, disodium EDTA, fragrance (parfum), methylisothiazolinone, neopentyl glycol diheptanoate, panthenol, pentylene glycol, phenoxyethanol, polyester-7, propanediol, styrene/acrylates copolymer, tocopheryl acetate, triethanolamine, water (aqua)

Other information

- protect this product from excessive heat and direct sun

QUESTIONS

Questions: Call 1-888-440-2563, Monday - Friday, 9:00 a.m. to 4:00 p.m. PT.